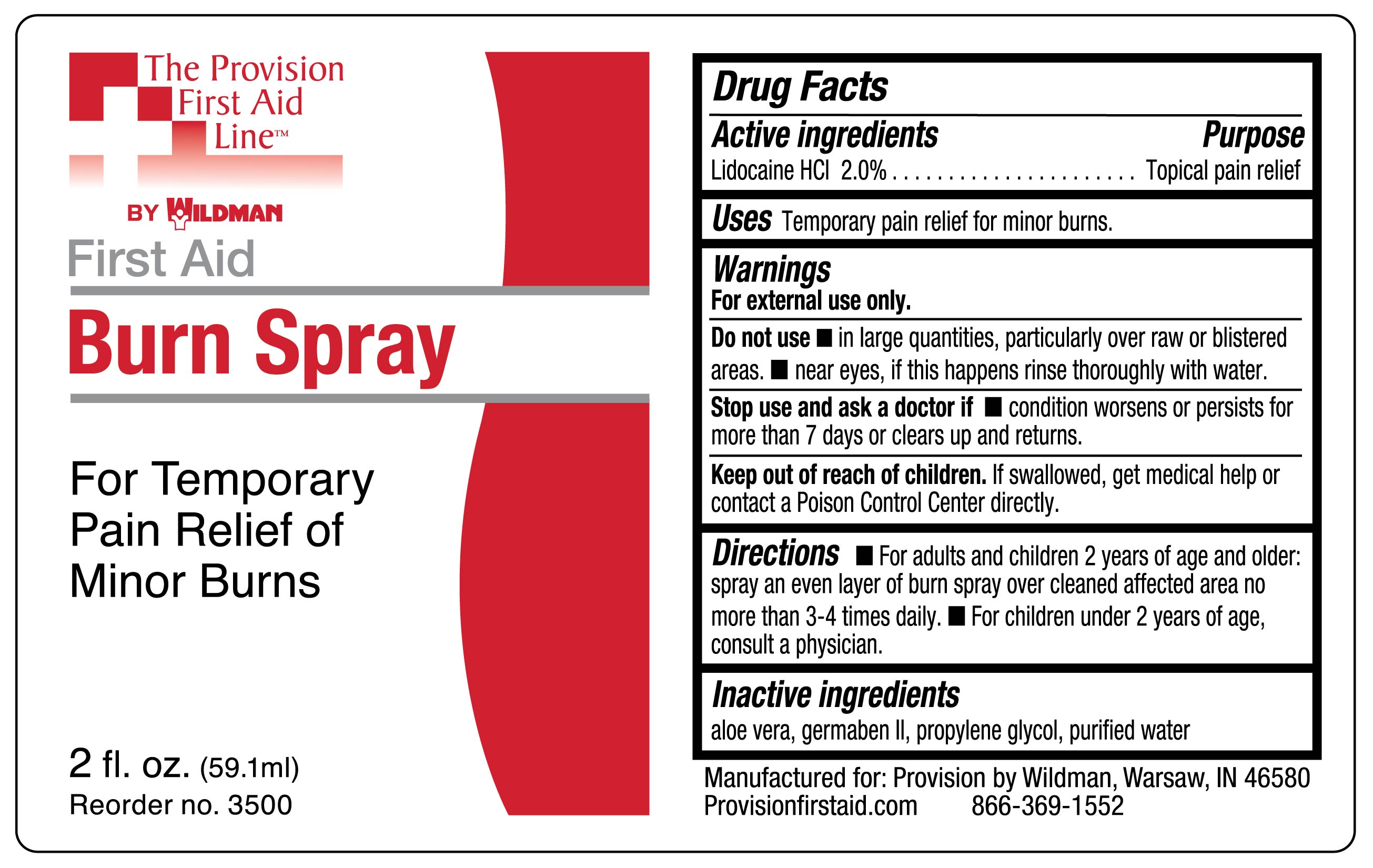 DRUG LABEL: Lidocaine Hydrochloride
NDC: 84269-3500 | Form: LIQUID
Manufacturer: Wildman Business Group
Category: otc | Type: HUMAN OTC DRUG LABEL
Date: 20240901

ACTIVE INGREDIENTS: LIDOCAINE HYDROCHLORIDE 20 mg/1 mL
INACTIVE INGREDIENTS: ALOE VERA LEAF; PROPYLENE GLYCOL; DIAZOLIDINYL UREA; WATER

84269-3500, Burn Spray

Drug Facts

Active ingredients

Lidocaine HCl 2.0%

Purpose

Topical pain relief

Uses

Temporary pain relief for minor burns

Warnings

For external use only

Do not use

- in large quantities, particularly over raw or blistered areas
- near eyes, if this happens rinse thoroughly with water

Stop use and ask a doctorif condition worsens or persists for more than 7 days or clears up and returns

- Keep out of reach of children.If swallowed get medical help or contact Poison Control Center right away

Directions

- for adults and children 2 years of age and older: spray an even layer of burn spray over cleaned affected area not more than 3-4 times daily
- for children under 2 years of age consult a physician

Inactive ingredients

aloe vera, germaben II, propylene glycol, purified water

Manufactured by SAFETEC OF AMERICA, Inc.

Buffalo, NY 14215 800-456-7077 www.safetec.com

PAIN RELIEF – Burn Spray
Safetec of America

Disclaimer: Most OTC drugs are not reviewed and approved by FDA, however they may be marketed if they comply with applicable regulations and policies. FDA has not evaluated whether this product complies.
----------

PRINCIPAL DISPLAY PANEL – 2 oz. bottle

Provision

First Aid
Burn Spray

For Temporary
Pain Relief of
Minor Burns

2fl. oz. (59.1ml)

Reorder no. 3500